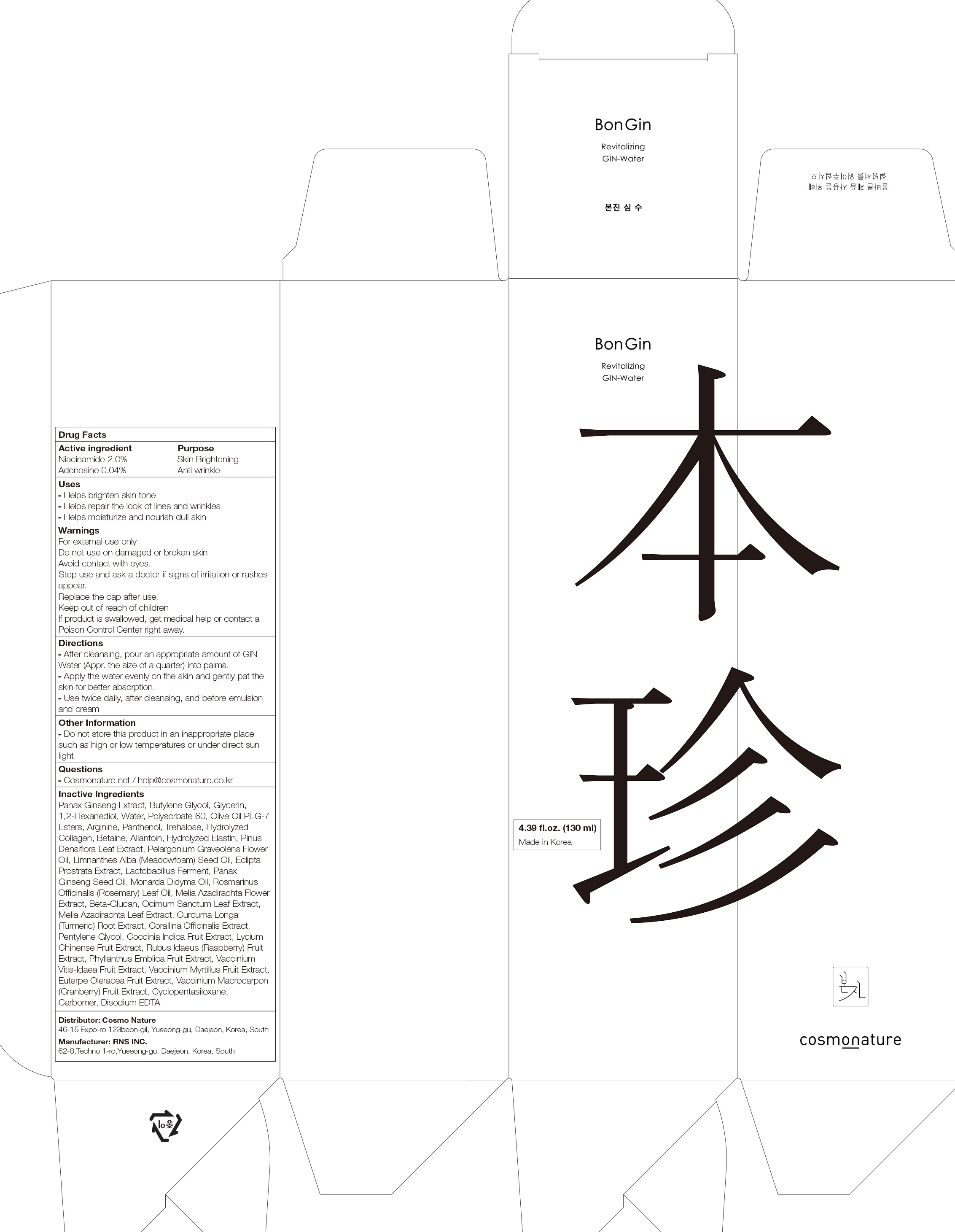 DRUG LABEL: BonGin Revitalizing GIN Water
NDC: 82492-010 | Form: LIQUID
Manufacturer: Cosmo Nature
Category: otc | Type: HUMAN OTC DRUG LABEL
Date: 20231213

ACTIVE INGREDIENTS: Niacinamide 2.0 g/100 mL; Adenosine 0.04 g/100 mL
INACTIVE INGREDIENTS: Butylene Glycol; Glycerin; 1,2-Hexanediol; Water

ACTIVE INGREDIENTS

Niacinamide 2.0%
Adenosine 0.04%

INACTIVE INGREDIENTS

Panax Ginseng Extract, Butylene Glycol, Glycerin, 1,2-Hexanediol, Water, Polysorbate 60, Olive Oil PEG-7 Esters, Arginine, Panthenol, Trehalose, Hydrolyzed Collagen, Betaine, Allantoin, Hydrolyzed Elastin, Pinus Densiflora Leaf Extract, Pelargonium Graveolens Flower Oil, Limnanthes Alba (Meadowfoam) Seed Oil, Eclipta Prostrata Extract, Lactobacillus Ferment, Panax Ginseng Seed Oil, Monarda Didyma Oil, Rosmarinus Officinalis (Rosemary) Leaf Oil, Melia Azadirachta Flower Extract, Beta-Glucan, Ocimum Sanctum Leaf Extract, Melia Azadirachta Leaf Extract, Curcuma Longa (Turmeric) Root Extract, Corallina Officinalis Extract, Pentylene Glycol, Coccinia Indica Fruit Extract, Lycium Chinense Fruit Extract, Rubus Idaeus (Raspberry) Fruit Extract, Phyllanthus Emblica Fruit Extract, Vaccinium Vitis-Idaea Fruit Extract, Vaccinium Myrtillus Fruit Extract, Euterpe Oleracea Fruit Extract, Vaccinium Macrocarpon (Cranberry) Fruit Extract, Cyclopentasiloxane, Carbomer, Disodium EDTA

PURPOSE

Skin Brightening
Anti wrinkle

WARNINGS

For external use only
Do not use on damaged or broken skin
Avoid contact with eyes.
Stop use and ask a doctor if signs of irritation or rashes appear.
Replace the cap after use.
Keep out of reach of children
If product is swallowed, get medical help or contact a Poison Control Center right away.

KEEP OUT OF REACH OF CHILDREN

Uses

■ Helps brighten skin tone
■ Helps repair the look of lines and wrinkles
■ Helps moisturize and nourish dull skin

Directions

■ After cleansing, pour an appropriate amount of GIN Water (Appr. the size of a quarter) into palms.
■ Apply the water evenly on the skin and gently pat the skin for better absorption.
■ Use twice daily, after cleansing, and before emulsion and cream

Other Information

■ Do not store this product in an inappropriate place such as high or low temperatures or under direct sun light

Questions

■ Cosmonature.net / help@cosmonature.co.kr